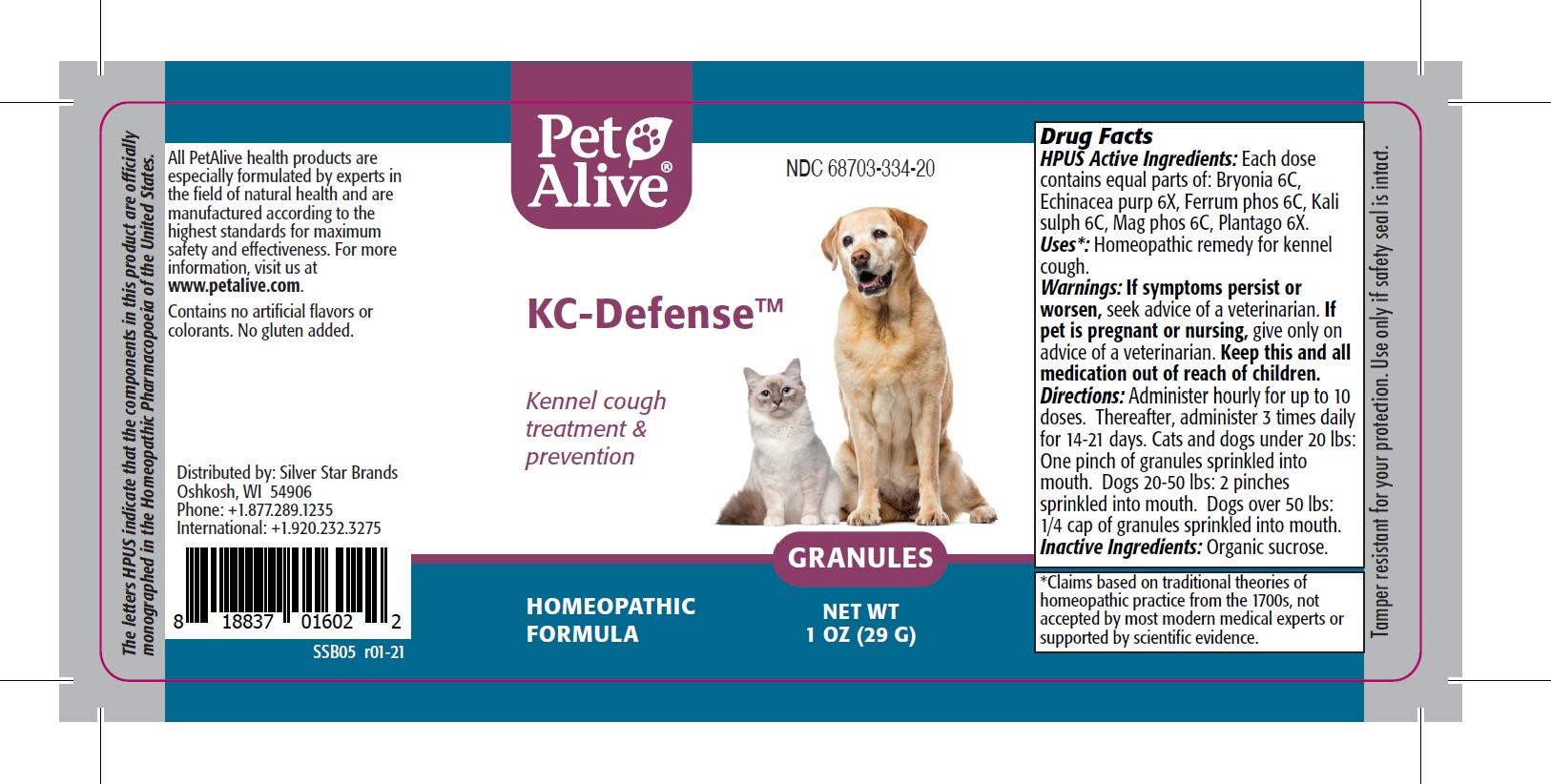 DRUG LABEL: PetAlive KC-Defense
NDC: 68703-334 | Form: GRANULE
Manufacturer: SILVER STAR BRANDS
Category: homeopathic | Type: OTC ANIMAL DRUG LABEL
Date: 20251216

ACTIVE INGREDIENTS: BRYONIA ALBA ROOT 6 [hp_C]/33 mg; ECHINACEA PURPUREA 6 [hp_X]/33 mg; FERROSOFERRIC PHOSPHATE 6 [hp_C]/33 mg; POTASSIUM SULFATE 6 [hp_C]/33 mg; MAGNESIUM PHOSPHATE, DIBASIC TRIHYDRATE 6 [hp_C]/33 mg; PLANTAGO MAJOR 6 [hp_X]/33 mg
INACTIVE INGREDIENTS: SUCROSE

PetAlive KC-Defense

PURPOSE

Kennel cough treatment and prevention

HPUS Active Ingredients:

Bryonia 6C
Echinacea purp 6X
Ferrum phos 6C
Kali sulph 6C
Mag phos 6C
Plantago 6X

INDICATIONS AND USAGE

Uses: Homeopathic remedy for kennel cough.

WARNINGS

Warnings: If symptoms persist or worsen, seek advice of a veterinarian.

PREGNANCY OR BREAST FEEDING

If pet is pregnant or nursing, give only on advice of a veterinarian.

KEEP OUT OF REACH OF CHILDREN

Keep this and all medication out of reach of children.

DOSAGE AND ADMINISTRATION

Directions: Administer hourly for up to 10 doses. Thereafter, administer 3 times daily for 14-21 days. Cats and dogs under 20 lbs: One pinch of granules sprinkled into mouth. Dogs 20-50 lbs: 2 pinches sprinkled into mouth. Dogs over 50 lbs: 1/4 cap of granules sprinkled into mouth.

Inactive Ingredients: organic sucrose.

INFORMATION FOR OWNERS/CAREGIVERS

The letters HPUS indicate that the components in this product are officially monographed in the Homeopathic Pharmacopoeia of the United States.

All PetAlive health products are especially formulated by experts in the field of natural health and are manufactured according to the highest standards for maximum safety and effectiveness. For more information, visit us at www.petalive.com.

Contains no artificial flavors or colorants. No gluten added.

Distributed by: Silver Star Brands
Oshkosh, WI 54906
Phone: +1.877.289.1235
International: +1.920.232.3275

STORAGE AND HANDLING

Tamper resistant seal for your protection. Use only if safety seal is intact.